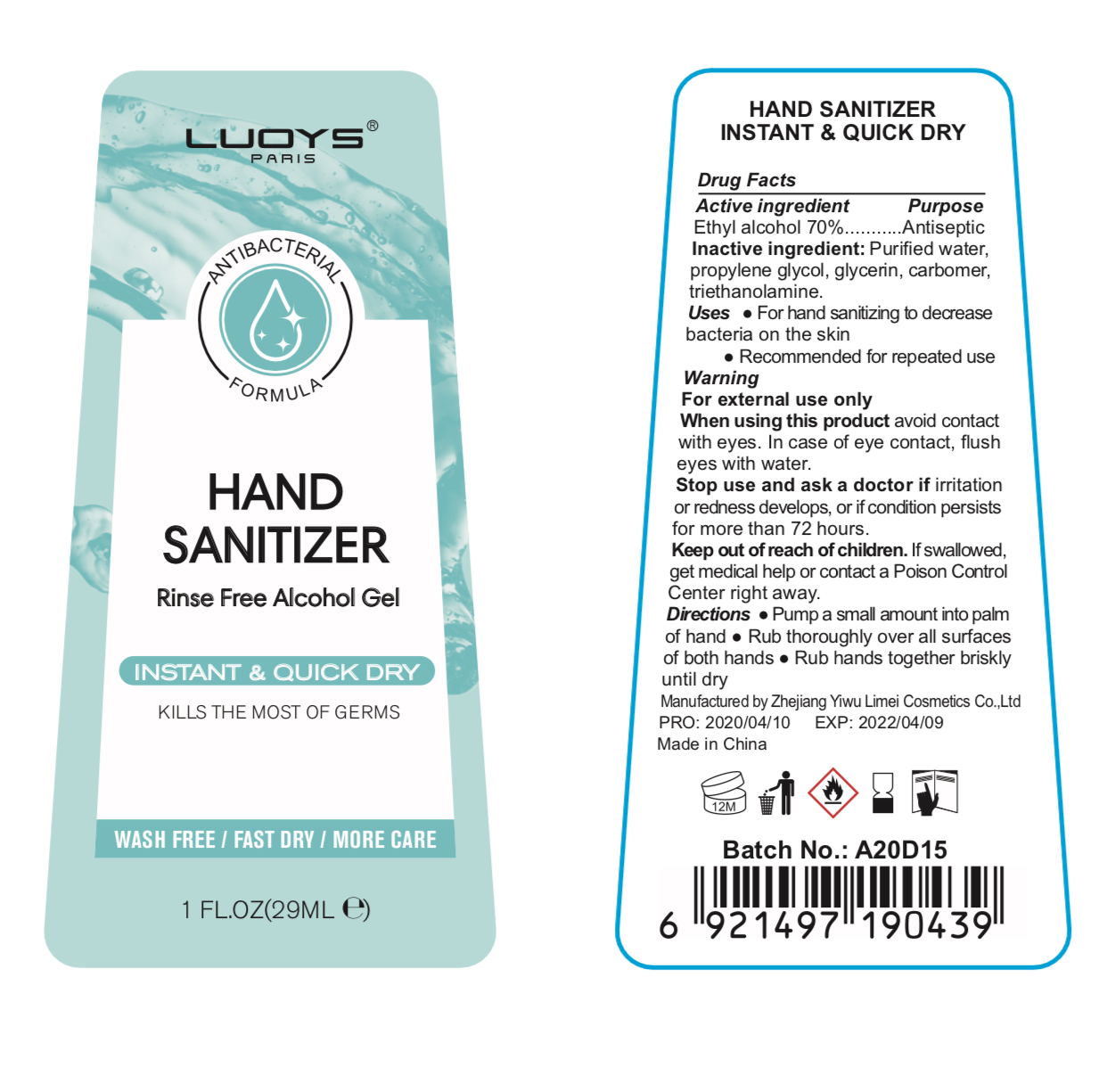 DRUG LABEL: LUOYS Hand Sanitier
NDC: 74765-001 | Form: GEL
Manufacturer: ZheJiang Yiwu Limei Cosmetics Co., Ltd
Category: otc | Type: HUMAN OTC DRUG LABEL
Date: 20200416

ACTIVE INGREDIENTS: ISOPROPYL ALCOHOL 75 mL/100 mL
INACTIVE INGREDIENTS: GLYCERIN; PROPYLENE GLYCOL; WATER; CARBOMER 934; TRIETHANOLAMINE SULFATE

NA

Active Ingredient(s)

Isopropyl Alcohol 75% v/v. Purpose: Antiseptic

Purpose

Antiseptic, Hand Sanitizer

Use

For hand sanitizing to help decrease bacteria on the skin

Recommended for repeated use

Warnings

For external use only. Flammable. Keep away from heat or flame

Do not use

- in children less than 2 months of age
- on open skin wounds

When using this product keep out of eyes, ears, and mouth. In case of contact with eyes, flush eyes with water.

Stop use and ask a doctor if irritation or redness develops, or if condition persists for more than 72 hours

Keep out of reach of children. If swallowed, get medical help or contact a Poison Control Center right away.

Directions

- Pump a small amount into palm of hands
- Rub thoroughly over all surface of both hands
- Rub hands together briskly untill dry

Other information

- Store between 15-30C (59-86F)
- Avoid freezing and excessive heat above 40C (104F)

Inactive ingredients

Water, propylene glycol, glycerin, carbomer, triethanolamine